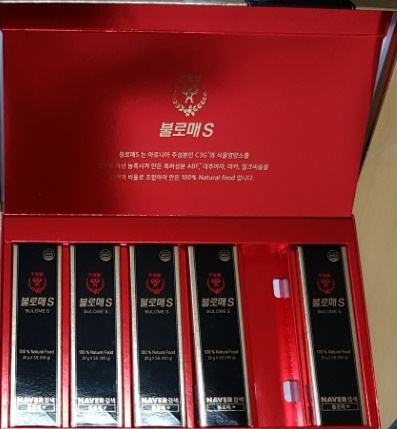 DRUG LABEL: BULOME S
NDC: 72173-0002 | Form: LIQUID
Manufacturer: JBKLAB Co., Ltd
Category: otc | Type: HUMAN OTC DRUG LABEL
Date: 20180924

ACTIVE INGREDIENTS: CHICORY LEAF 15.4 g/100 g
INACTIVE INGREDIENTS: ARONIA MELANOCARPA FRUIT

ACTIVE INGREDIENT

chicory extract

INACTIVE INGREDIENT

honey, aronia extract powder, enzyme treated stevia

PURPOSE

in the fruit of Aronia, a large amount of red anthraanthocyanin is contained, which is very powerful antioxidant. It acts as a powerful cell signaling molecule (CSM), immunity enhancing action, blood flow improving action, and stem cell activating action were excellent.

WARNINGS

1. Open the pouch slowly so that the contents may come off when opening.
2. The edge of the pouch is sharp, so be careful not to let your skin dry when you are eating or carrying it.
3. Do not heat the microwave oven as it is pouch packaging.

Keep out of reach of children.

INDICATIONS AND USAGE

Take 1 pouch (20g) once or twice a day

DOSAGE AND ADMINISTRATION

for oral use only